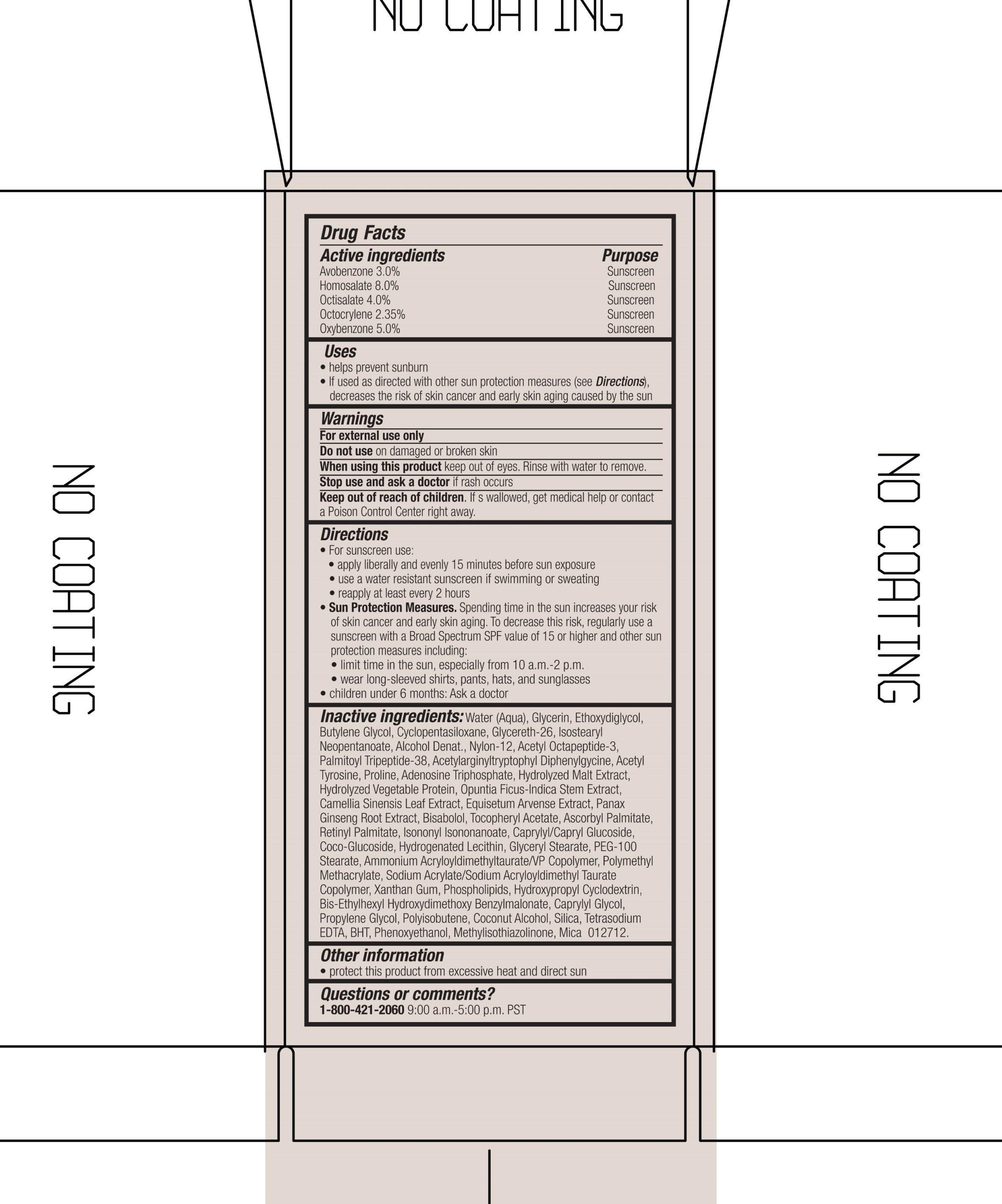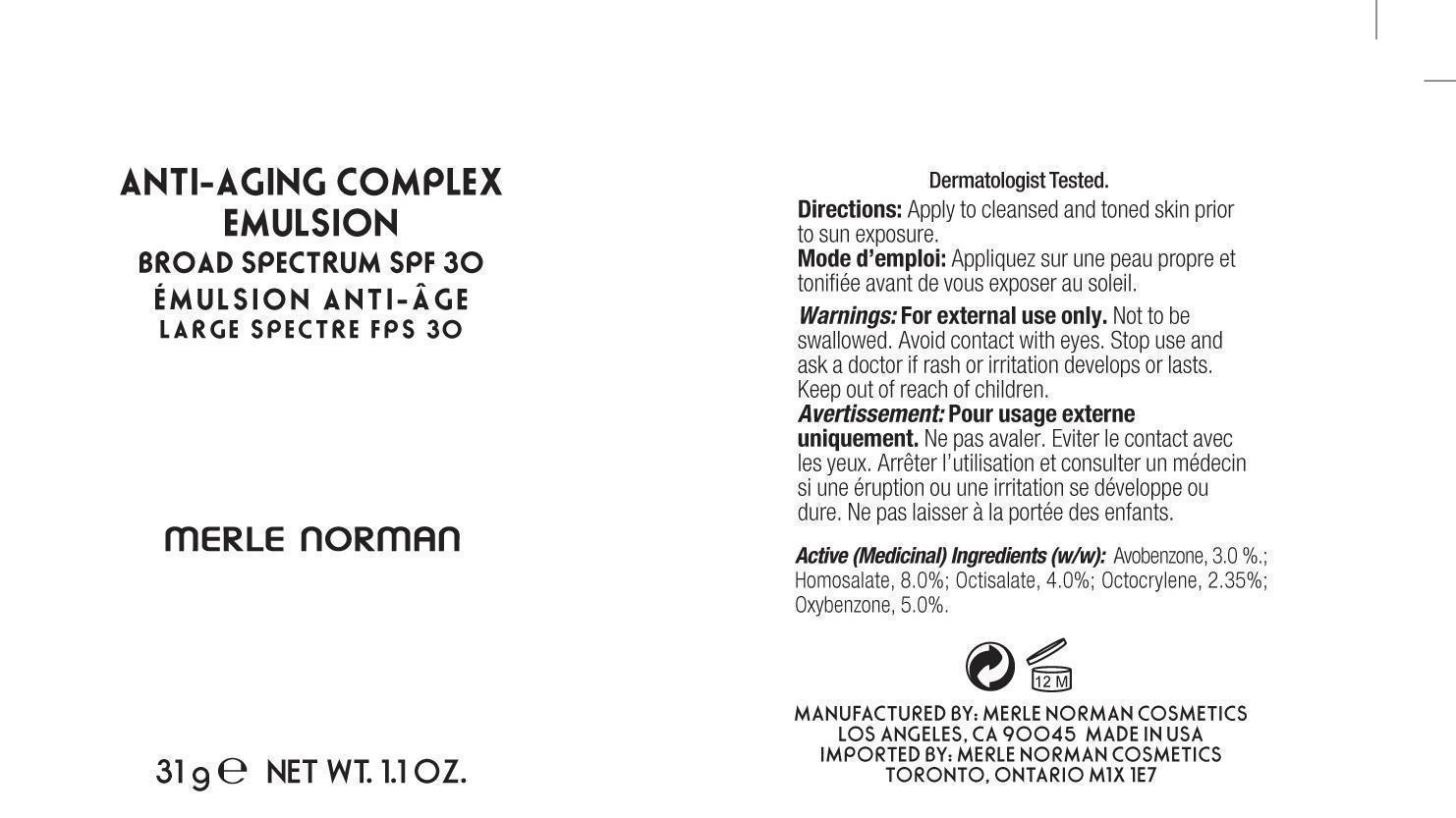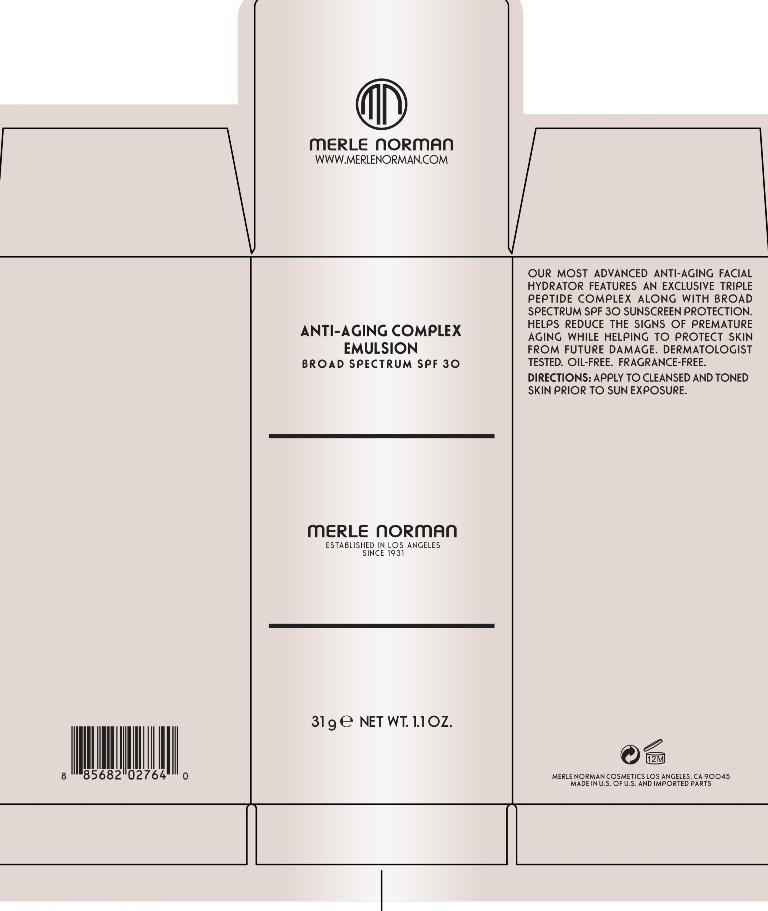 DRUG LABEL: Anti-Aging Complex SPF 30
NDC: 57627-149 | Form: EMULSION
Manufacturer: Merle Norman Cosmetics, Inc.
Category: otc | Type: HUMAN OTC DRUG LABEL
Date: 20200127

ACTIVE INGREDIENTS: AVOBENZONE 0.93 g/31 g; HOMOSALATE 2.48 g/31 g; OCTISALATE 1.24 g/31 g; OCTOCRYLENE 0.729 g/31 g; OXYBENZONE 1.55 g/31 g
INACTIVE INGREDIENTS: WATER; GLYCERIN; DIETHYLENE GLYCOL MONOETHYL ETHER; BUTYLENE GLYCOL; CYCLOMETHICONE 5; GLYCERETH-26; ISOSTEARYL NEOPENTANOATE; NYLON-12; ACETYL OCTAPEPTIDE-3; N-ACETYLTYROSINE; PROLINE; ADENOSINE TRIPHOSPHATE; BARLEY MALT SYRUP; OPUNTIA FICUS-INDICA STEM; GREEN TEA LEAF; EQUISETUM ARVENSE TOP; ASIAN GINSENG; LEVOMENTHOL; .ALPHA.-TOCOPHEROL ACETATE; ASCORBYL PALMITATE; VITAMIN A PALMITATE; ISONONYL ISONONANOATE; CAPRYLYL/CAPRYL OLIGOGLUCOSIDE; COCO GLUCOSIDE; HYDROGENATED SOYBEAN LECITHIN; GLYCERYL MONOSTEARATE; PEG-100 STEARATE; AMMONIUM ACRYLOYLDIMETHYLTAURATE/VP COPOLYMER; SODIUM ACRYLATE/SODIUM ACRYLOYLDIMETHYLTAURATE COPOLYMER (4000000 MW); XANTHAN GUM; EGG PHOSPHOLIPIDS; BIS-ETHYLHEXYL HYDROXYDIMETHOXY BENZYLMALONATE; CAPRYLYL GLYCOL; PROPYLENE GLYCOL; POLYISOBUTYLENE (1000 MW); COCONUT ALCOHOL; SILICON DIOXIDE; EDETATE SODIUM; BUTYLATED HYDROXYTOLUENE; PHENOXYETHANOL; METHYLISOTHIAZOLINONE; MICA

Anti-Aging Complex Emulsion Broad Spectrum SPF 30

Active Ingredients purpose

Avobenzone 3.0% Sunscreen

Homosalate 8.0% Sunscreen

Octisalate 4.0 % Sunscreen

Octocrylene 2.35% Sunscreen

Oxybenzone 5.0% Sunscreen

Uses

Helps prevent sunburn

If used as directed with other sun protection measures (see directions), decreases the risk of skin cancer and early skin aging caused by the sun.

Keep out of reach of children. If swallowed, get medical help or contact a Poison Control Center right away.

Stop use and ask a doctor if rash occurs.

Warnings

For external use only

Do not use on damaged or broken skin

When using this product, keep out of eyes. Rinse with water to remove.

Directions

for Sunscreen use

-Apply Liberally and evenly 15 minutes before sun exposure

-Use a water resistant sunscreen if swimming or sweating

-Reapply at least every 2 hours

Sun Protection Measures. Spending time in the sun increases your risk of skn cancer and early skin aging. To decrease this risk, regularly use a sunscreen with a Broad Spectrum value of 15 or higher and other sun protection measures including:

-limit time in the sun, especially from 10 a.m. to 2 p.m.

- wear long-sleeved shirts, pants, hats and and sunglasses

Children under 6 months: Ask a doctor

INACTIVE INGREDIENT

Inactive ingredients: water(aqua), glycerin, ethoxydiglycol, butylene glycol, cyclopentasiloxane, glycereth-26, isostearyl neopentanoate, alcohol denat., nylon-12, acetyl octapeptide-3, palmitoyl tripeptide-38, acetylarginyltryptophyl diphenylglycine, acetyl tyrosine, proline, adenosine triphosphate, hydrolyzed malt extract, hydrolyzed vegetable protein, optunia ficus-indica stem extract, camellia sinensis leaf extract, equisetum arvense extract, panax ginseng root extract, bisabolol, tocopheryl acetate, ascorbyl palmitate, retinyl palmitate, isononyl isononanoate, caprylyl/capryl glucoside, coco-glucoside, hydrogenated lecithin, glyceryl stearate, peg-100 stearate, ammonium acryloyldimethyltaurate/VP copolymer, polymethyl methacrylate, sodium acrylate/sodium acryloyldimethyl taurate copolymer, xanthan gum, phospholipids, hydroxypropyl cyclodextrin, bis-ethylhexyl hydroxydimethoxy benzylmalonate, caprylyl glycol, propylene glycol, polyisobutene, coconut alcohol, silica, tetrasodium EDTA, BHT, phenoxyethanol, methylisothiazolinone, mica

PACKAGE LABEL

Anti-Aging Complex Emulsion

Broad Spectrum SPF 30

Merle Norman

Established in Los Angeles since 1931

31g Net Wt. 1.1 oz